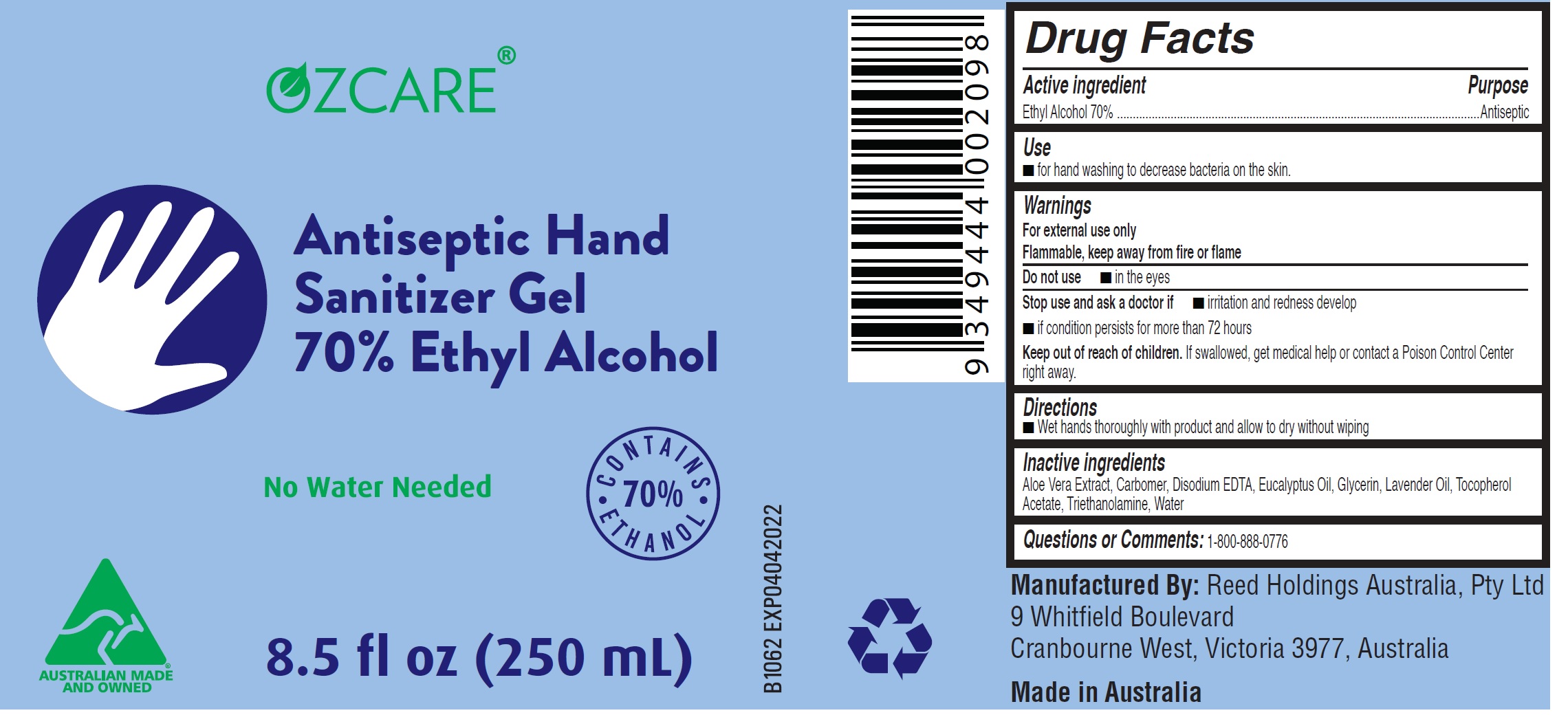 DRUG LABEL: Ozcare Antiseptic Hand Sanitizer
NDC: 75584-002 | Form: GEL
Manufacturer: Reed Holdings Australia, Pty. Ltd.
Category: otc | Type: HUMAN OTC DRUG LABEL
Date: 20200723

ACTIVE INGREDIENTS: ALCOHOL 0.7 mL/1 mL
INACTIVE INGREDIENTS: ALOE VERA LEAF; EDETATE DISODIUM ANHYDROUS; EUCALYPTUS OIL; GLYCERIN; LAVENDER OIL; .ALPHA.-TOCOPHEROL ACETATE; TROLAMINE; WATER

Ozcare Antiseptic Hand Sanitizer Gel

Active ingredient

Ethyl Alcohol 70%

Purpose

Antiseptic

Use

- for hand washing to decrease bacteria on the skin.

Warnings

For external use only
Flammable, keep away from fire or flame

Do not use

- in the eyes

Stop use and ask a doctor if

- irritation and redness develop
- if condition persists for more than 72 hours

Keep out of reach of children.

If swallowed, get medical help or contact a Poison Control Center
right away.

Directions

- Wet hands thoroughly with product and allow to dry without wiping

Inactive ingredients

Aloe Vera Extract, Disodium EDTA, Eucalyptus Oil, Glycerin, Lavender Oil, Tocopherol Acetate, Triethanolamine, Water

Questions or Comments:

1-800-888-0776